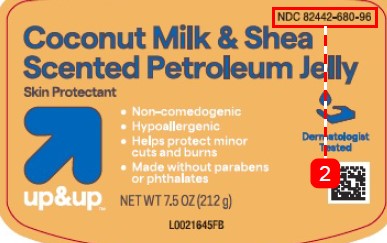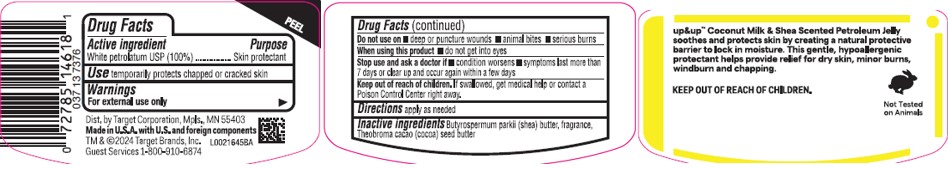 DRUG LABEL: Coconut Milk and Shea Petroleum Jelly
NDC: 82442-680 | Form: JELLY
Manufacturer: Target Corporation
Category: otc | Type: HUMAN OTC DRUG LABEL
Date: 20260218

ACTIVE INGREDIENTS: PETROLATUM 1 g/1 g
INACTIVE INGREDIENTS: SHEA BUTTER; COCOA BUTTER

Up & Up 680.000/680AA
Coconut Milk and Shea Scented Petroleum Jelly

Active ingredient

White petrolatum USP (100%)

Purpose

Skin protectant

Use

- temporarily protects chapped or cracked skin

Warnings

For external use only

Do not use on

- deep or puncture wounds
- animal bites
- serious burns

When using this product

- do not get into eyes

Stop use and ask a doctor if

- condition worsens
- symptoms last more than 7 days or clear up and occur again within a few days

Keep out of reach of children.

If swallowed, get medical help or contact a Poison Control Center right away.

Directions

apply as needed

Inactive Ingredients

Butyrospermum parkii (shea) butter, fragrance, Theobroma cacao (cocoa) seed butter

Claims

up&up™ Coconut Milk & Shea Scented Petroleum Jelly soothes and protects skin by creating a natural protective barrier to lock in moisture. This gentle, hypoallergenic protectant helps provide relief for dry skin, minor burns, windburn and chapping.

KEEP OUT OF REACH OF CHILDREN

Not Tested on Animals

Adverse Reactions

Distributed by Target Corporporation, Mpls., MN 55403

Made in U.S.A with U.S. and foreign components

TM & ©2024 Target Brands, Inc.

Guest Services 1-800-910-6874

Principal display panel

NDC 82442-680-96

Coconut Milk & Shea Scented Petroleum Jelly

Skin Protectant

- Non-comedogenic
- Hypoallergenic
- Helps protect minor cuts and burns
- Made without parabens or phthalates

Dermatologist Tested

up & up™

NET WT 7.5 OZ (212 g)